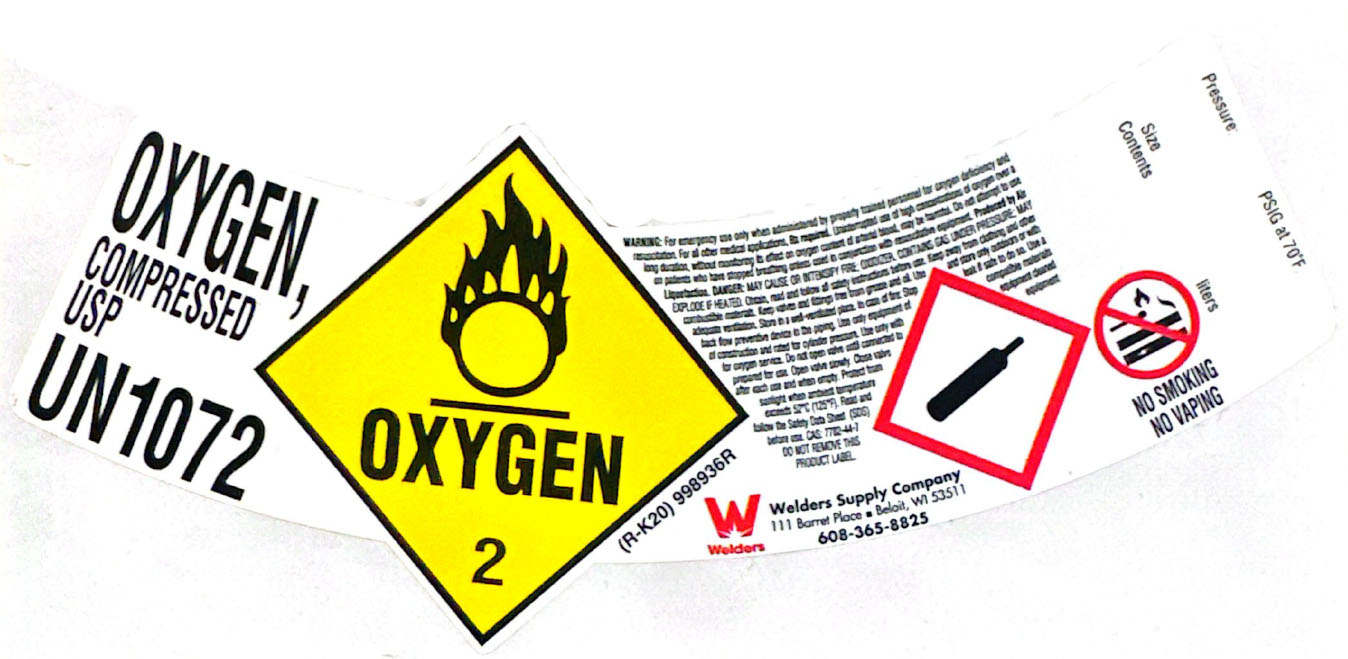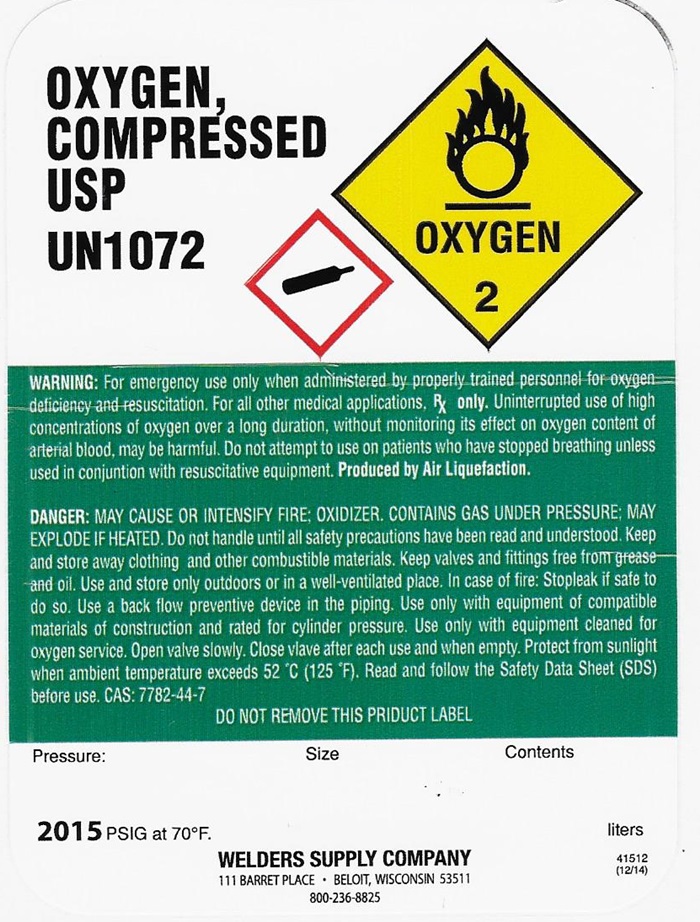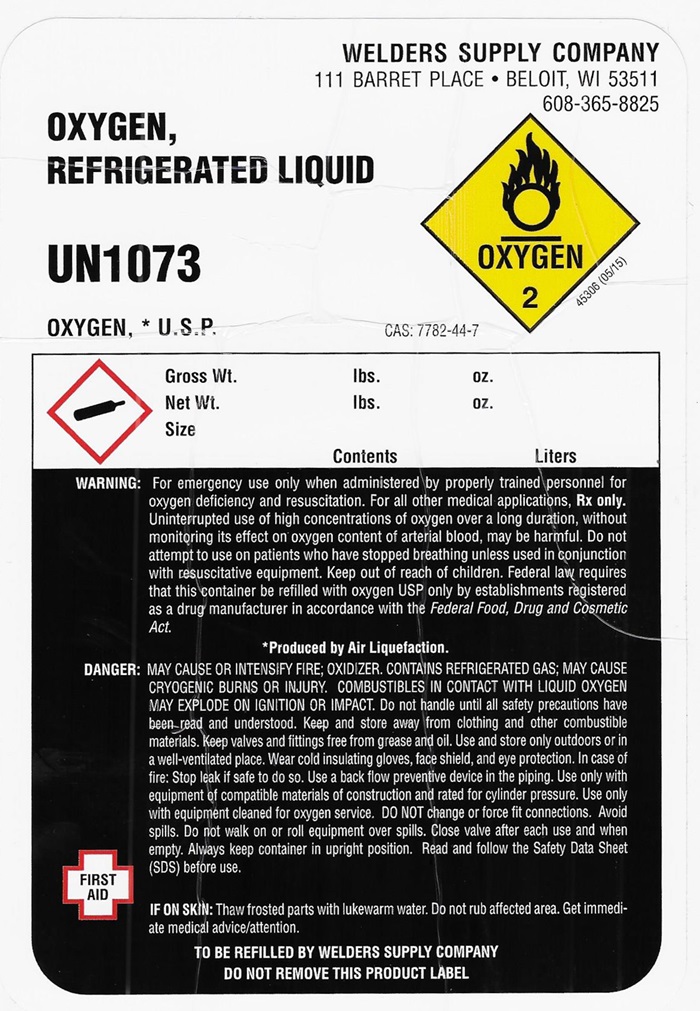 DRUG LABEL: OXYGEN
NDC: 11999-001 | Form: GAS
Manufacturer: Welders Supply Company
Category: prescription | Type: HUMAN PRESCRIPTION DRUG LABEL
Date: 20250706

ACTIVE INGREDIENTS: OXYGEN 992 mL/1 L

Oxygen

REFRIGERATED LIQUID OXYGEN USP LABEL

WELDERS SUPPLY COMPANY

111 BARRET PLACE • BELOIT, WI 53511

608-365-8825

OXYGEN,

REFRIGERATED LIQUID

UN 1073

OXYGEN, *U.S.P.

CAS: 7782-44-7

OXYGEN 2 45306 (05/15)

Gross Wt. lbs. oz.

Net Wt. lbs. oz.

Size Contents Liters

Rx ONLY. WARNING: For emergency use only when administered by properly trained personnel for oxygen deficiency and resuscitation. For all other medical applications, Rx only.

Uninterrupted use of high concentrations of oxygen over a long duration, without monitoring its effect on oxygen content of arterial blood, may be harmful. Do not attempt to use on patients who have stopped breathing unless used in conjunction of resuscitative equipment.

Produced by Air Liquefaction.

DANGER: MAY CAUSE OR INTENSIFY FIRE; OXIDER, CONTAINS REFRIGERATED GAS; MAY CAUSE CRYOGENIC BURNS OR INJURY. COMBUSTIBELS IN CONTACT WITH LIQUID OXYGEN MAY EXPLODE ON IGNITION OR IMPACT.

Do not handle until all safety precautions have been read and understood. Keep and store away from clothing and other combustible materials. Keep valves and fittings free from grease and oil. Use and store only outdoors or in a well-ventilated place. Wear cold insulating gloves, face shield, and eye protection. In case of fire: Stop leak if safe to do so. Use a back flow preventive device in the piping. Use only the equipment of compatible materials equipment cleaned for oxygen service. DO NOT change or force fit connections. Avoid spills. Do not walk on or roll equipment over spills. Close valve after each use and when empty. Always keep container in upright position.

Read and follow the Safety Data Sheet (SDS) before use.

FIRST AID FIRST AID: IF ON SKIN: Thaw affected parts with lukewarm water. Do not rub affected area. Get immediate medical advice/attention.

TO BE REFILLED BY WELDERS SUPPLY COMPANY

DO NOT REMOVE THIS PRODUCT LABEL

HP OXYGEN USP SHOULDER LABEL

OXYGEN, COMPRESSED USP UN 1072

OXYGEN 2

(R-K20) 998936R

WARNING: For emergency use only when administered by properly trained personnel for oxygen deficiency and resuscitation. For all other medical applications, Rx required. Uninterrupted use of high concentrations of oxygen over a long duration, without monitoring its effect on oxygen content of arterial blood, may be harmful. Do not attempt to use on patients who have stopped breathing unless used in conjunction with resuscitative equipment. Produced by Air Liquefaction. DANGER: MAY CAUSE OR INTENSIFIRE FIRE; OXIDIZER. CONTAINS GAS UNDER PRESSURE; MAY EXPLODE IF HEATED. Obtain, read and follow all safety instructions before use. Keep away from clothing and other combustible materials. Keep valves and fittings free from grease and oil. Use and store only outdoors or with adequate ventilation. Store in a well-ventilated place. In case of fire: Stop leak if safe to do so. Use a back flow preventive device in the piping. Use only qequipment of compatible materials of construction and rated for cylinder pressure. Use only with equipment cleaned for oxygen service. Do not open valve until connected to equipment prepared for use. Open valve slowly. Close valve after each use and when empty. Protect form sunlight when ambient temperature exceeds 52°C (125°F). Read and follow the Safety Data Sheet (SDS) before use. CAS 7782-44-7

DO NOT RMOVE THIS PRODUCT LABEL

WELDERS SUPPLY COMPANY

111 BARRET PLACE • BELOIT, WI 53511

608-365-8825

Pressure: PSIG at 70OF

Size

Contents liters

NO SMOKING

NO VAPING

HP OXYGEN USP LABEL

OXYGEN, COMPRESSED USP

UN 1072

OXYGEN2

WARNING: For emergency use only when administered by properly trained personnel for oxygen deficiency and resuscitation. For all other medical applications, Rx only. Uninterrupted use f high concentrations of oxygen over a long duration, without monitoring its effect on oxygen content of arterial blood, may be harmful. Do not attempt to use on patients who have stopped breathing unless used in conjunction with resuscitative equipment. PRODUCED BY AIR LIQUEFACTION

DANGER: MAY CAUSE OR INTENSIFY FIRE; OXIDIZER. CONTAINS GAS UNDER PRESSURE; MAY EXPLODE IF HEATED. Do not handle until all safety precautions have been read and understood. Keep and store away from clothing and other combustible materials. Keep valves and fittings free from grease and oil. Use and store only outdoors or in a well-ventilated place. In case of fire: Stop leak if safe to do so. Use a backflow preventive device in the piping. Use only with equipment of compatible materials of construction and rated for cylinder pressure. Use only with equipment cleaned for oxygen service. Open valve slowly. Close valve after each use and when empty. Protect from sunlight when ambient temperature exceeds 52°C (125° F). Read and follow the Safety Data Sheet (SDS) before use. CAS 7782-44-7

DO NOT REMOVE THIS LABEL

Pressure: Size Contents:

2015 PSIG at 70OF liters

WELDERS SUPPLY COMPANY

111 BARRET PLACE • BELOIT, WI 53511

1/800-236-8825